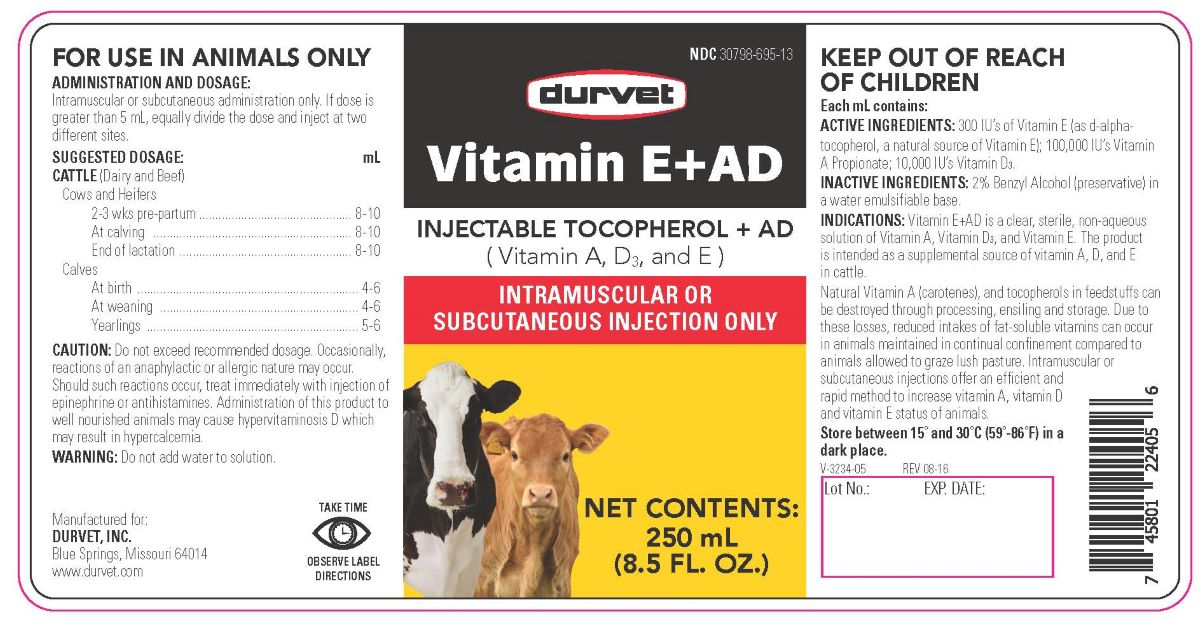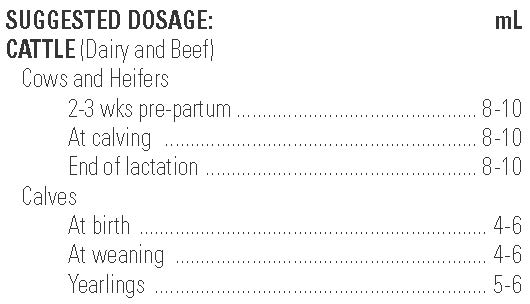 DRUG LABEL: EmulsiVit E AD
NDC: 30798-695 | Form: INJECTION
Manufacturer: Durvet, Inc.
Category: animal | Type: OTC ANIMAL DRUG LABEL
Date: 20231211

ACTIVE INGREDIENTS: .ALPHA.-TOCOPHEROL, D- 201 mg/1 mL; VITAMIN A 3.6 mg/1 mL; VITAMIN D 2.5 mg/1 mL

Vitamin E+AD

INDICATIONS AND USAGE

Vitamin E+AD

Injectable Tocopherol + AD

(Vitamin A, D3, and E)

INTRAMUSCULAR OR SUBCUTANEOUS INJECTION ONLY

Indications: Vitamin E+AD AD is a clear, sterile, non-aqueous solution of vitamin A,vitamin D3,and vitamin E. The product is intended as a supplemental source of vitamins A, D and E in cattle.

Natural vitamin A (carotenes), and tocopherols can be destroyed in feedstuffs through processing, ensiling and storage. Due to these losses, reduced intakes of fat-soluble vitamins can occur in animals maintained in continual confinement compared to animals allowed to graze in lush pasture. Intramuscular or subcutaneous injections offer an efficient and rapid method to increase vitamin A, vitamin D and Vitamin E status of animals.

Each mL contains:

ACTIVE INGREDIENTS: 300IU's vitamin E (as d-alpha-tocopherol, a natural source of vitamin E); 100,000 IU's Vitamin A Propionate:; 10,000 IU's Vitamin D3.

INACTIVE INGREDIENTS: 2% benzyl alcohol (preservative) in a water emulsifiable base.

Caution:

Do not exceed recommended dosage. Occasionally, reactions of an anaphylactic or allergic nature may occur. Should such reactions occur, treat immediately with injection of epinephrine or antihistamines. Administration of this product to well nourished animals may cause hypervitaminosis D which may result in hypercalcemia.

Warning:

Do not add water to solution.

FOR USE IN ANIMALS ONLY

KEEP OUT OF REACH OF CHILDREN

TAKE TIME

OBSERVE LABEL DIRECTIONS

STORAGE AND HANDLING

Store between 15°—30°C (59°—86°F) in a dark place.

ADMINISTRATION AND DOSAGE:

Intramuscular or Subcutaneous Administration Only. May be repeated. If dose is greater than 5 mL, equally divide the dose and inject at two different sites.